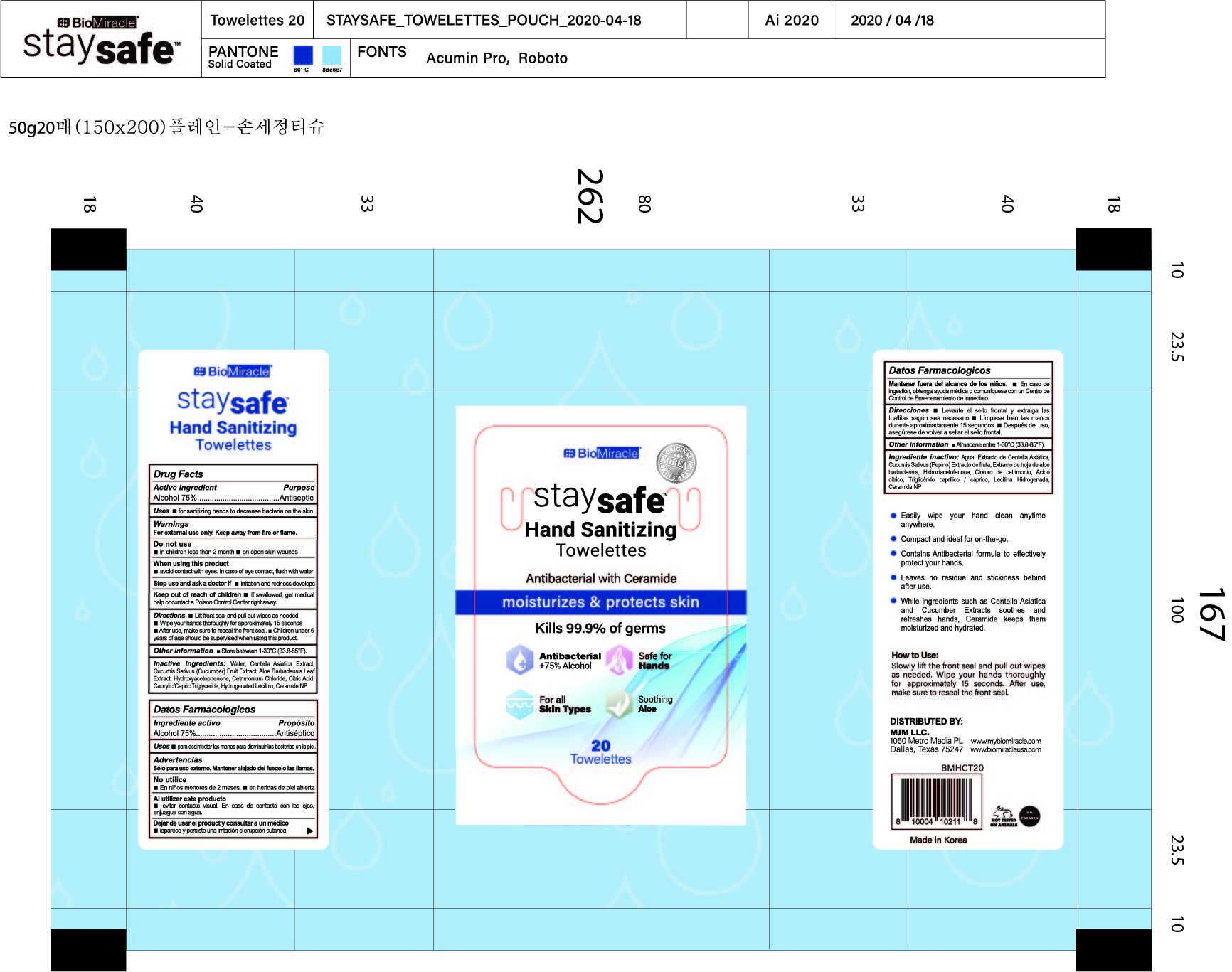 DRUG LABEL: BioMiracle staysafe Hand Sanitizing Towelettes
NDC: 77978-075 | Form: CLOTH
Manufacturer: MJM SOURCING, LLC
Category: otc | Type: HUMAN OTC DRUG LABEL
Date: 20200810

ACTIVE INGREDIENTS: ALCOHOL 0.75 1/1 1
INACTIVE INGREDIENTS: CETRIMONIUM CHLORIDE; WATER; CENTELLA ASIATICA; CITRIC ACID MONOHYDRATE; CUCUMBER JUICE; ALOE VERA LEAF; HYDROXYACETOPHENONE; CERAMIDE NP; MEDIUM-CHAIN TRIGLYCERIDES; HYDROGENATED SOYBEAN LECITHIN

[Manufacturer: Dang ho paper Inc.] Labeler : MJM SOURCING, LLC | 77978-075-20
BioMiracle staysafe Hand Sanitizing Towelettes 20 ct.